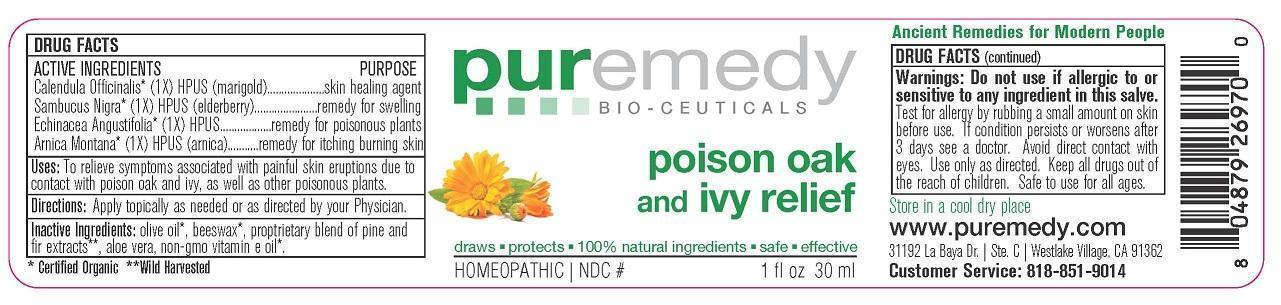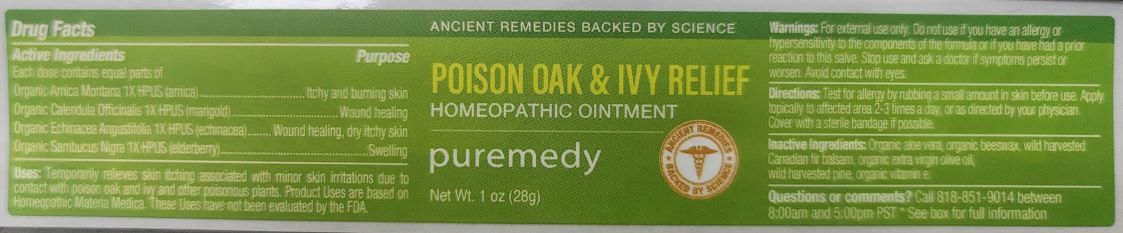 DRUG LABEL: POISON OAK AND IVY RELIEF
NDC: 52810-702 | Form: SALVE
Manufacturer: PUREMEDY
Category: homeopathic | Type: HUMAN OTC DRUG LABEL
Date: 20240111

ACTIVE INGREDIENTS: CALENDULA OFFICINALIS FLOWER 1 [hp_X]/100 mL; SAMBUCUS NIGRA FLOWER 1 [hp_X]/100 mL; ECHINACEA ANGUSTIFOLIA 1 [hp_X]/100 mL; ARNICA MONTANA 1 [hp_X]/100 mL
INACTIVE INGREDIENTS: YELLOW WAX; CANADA BALSAM; ALOE VERA LEAF; .ALPHA.-TOCOPHEROL; OLIVE OIL

POISON OAK AND IVY RELIEF (52810-702)

ACTIVE INGREDIENTS

ORG. CALENDULA OFFICINALIS (1X) HPUS) (MARIGOLD)

ORG. SAMBUCUS NIGRA (1X) HPUS (ELDER BARK AND FLOWER)

ORG. ECHINACEA ANGUSTIFOLIA (1X) HPUS (ECHINACEA)

ORG. ARNICA MONTANA (1X) HPUS (ARNICA)

PURPOSE

SKIN HEALING AGENT

REMEDY FOR SWELLING

REMEDY FOR POISONOUS PLANTS

REMEDY FOR ITCHING BURNING SKIN

INDICATIONS AND USAGE

USES: TO RELIEVE SYMPTOMS ASSOCIATED WITH PAINFUL SKIN ERUPTIONS DUE TO CONTACT WITH POISON OAK AND IVY, AS WELL AS OTHER POISONOUS PLANTS.

DOSAGE AND ADMINISTRATION

DIRECTIONS: APPLY TOPICALLY AS NEEDED OR AS DIRECTED BY YOUR PHYSICIAN.

INACTIVE INGREDIENT

INACTIVE INGREDIENTS: ORG. OLIVE OIL, ORG. BEESWAX, PROPRIETARY BLEND OF PINE AND FIR EXTRACTS, ALOE VERA, ORG. NON-GMO VITAMIN E OIL

WARNINGS

WARNINGS: DO NOT USE IF ALLERGIC TO OR SENSITIVE TO ANY INGREDIENT IN THIS SALVE. TEST FOR ALLERGY BY RUBBING A SMALL AMOUNT ON SKIN BEFORE USE. IF CONDITION PERSISTS OR WORSENS AFTER 3 DAYS SEE A DOCTOR. AVOID DIRECT CONTACT WITH EYES. USE ONLY AS DIRECTED. KEEP ALL DRUGS OUT OF USE OF CHILDREN. SAFE TO USE FOR ALL AGES.

KEEP ALL DRUGS OUT OF REACH OF CHILDREN.

STORAGE AND HANDLING

STORE IN A COOL DRY PLACE OR REFRIGERATE.

QUESTIONS

CUSTOMER SERVICE 818-851-9014